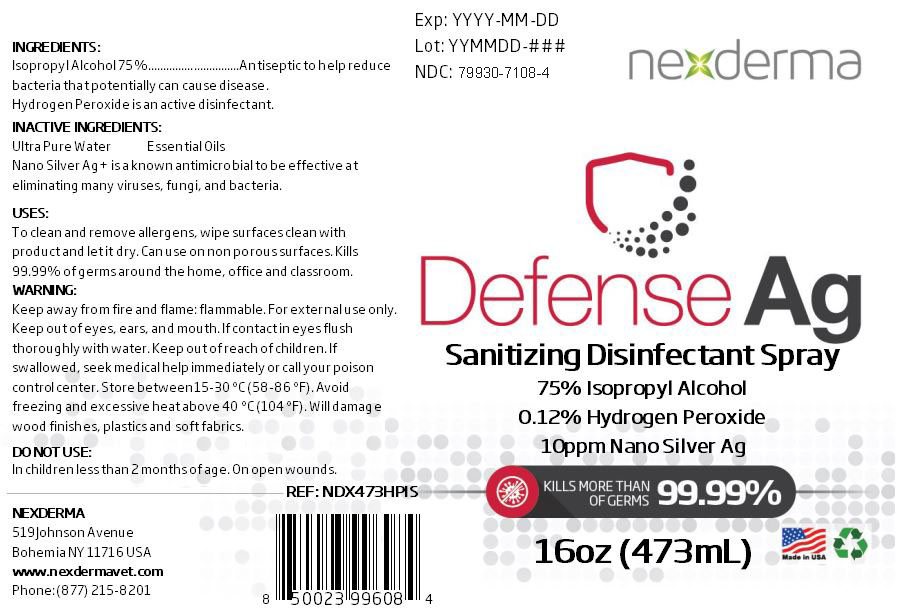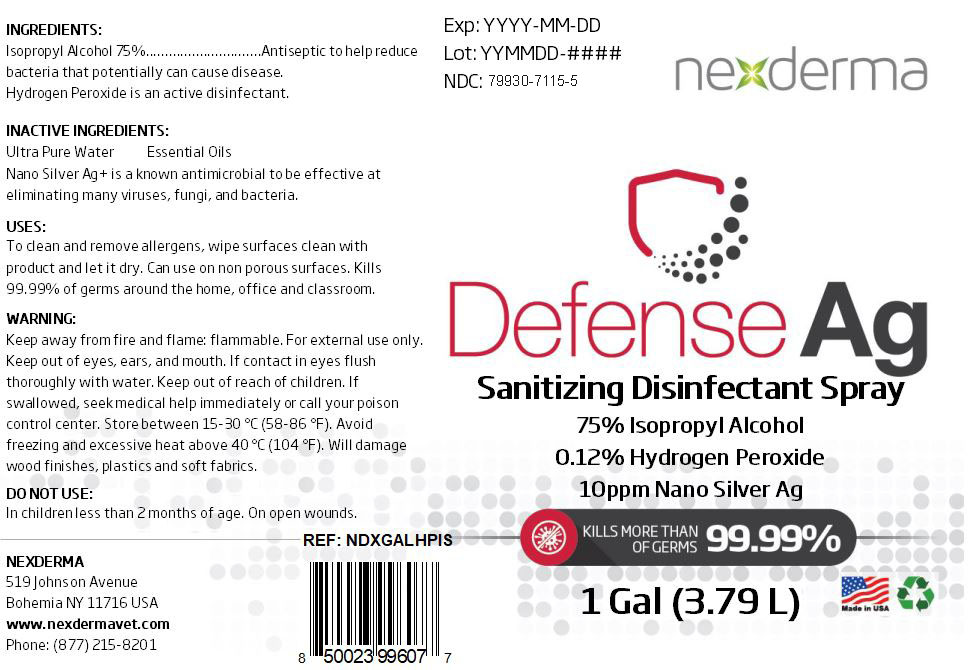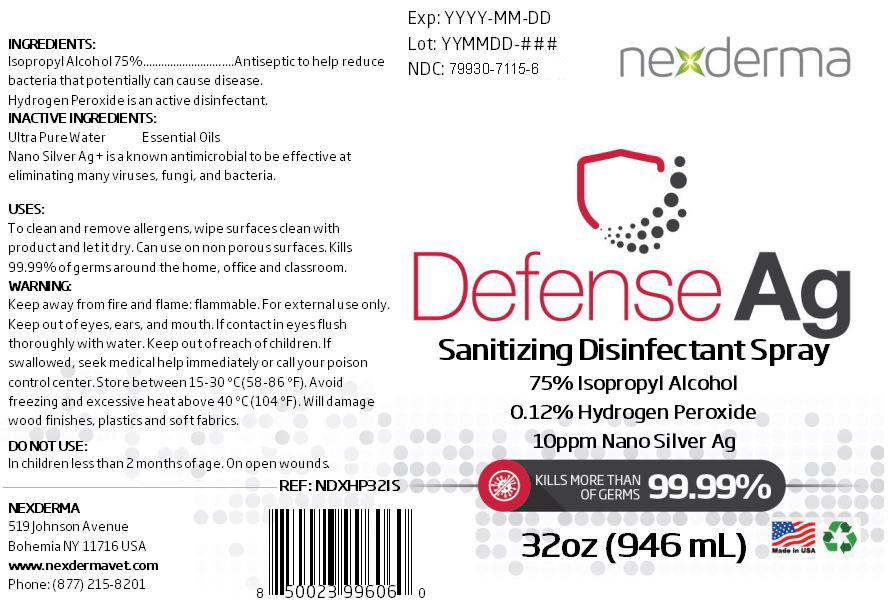 DRUG LABEL: Defense AG Disinfectant
NDC: 79930-7115 | Form: SPRAY
Manufacturer: Nexderma
Category: otc | Type: HUMAN OTC DRUG LABEL
Date: 20201104

ACTIVE INGREDIENTS: HYDROGEN PEROXIDE 0.125 mL/100 mL; ISOPROPYL ALCOHOL 75 mL/100 mL
INACTIVE INGREDIENTS: SILVER 0.2 mL/100 mL; WATER

Defense AG Disinfectant ISO - New

Active Ingredient(s)

Isopropyl Alcohol 75% v/v. Purpose: Antiseptic to help reduce bacteria that potentially can caused disease.

Hydrogen Peroxide

Inactive ingredients

ultra pure water, Nano Silver Ag+

Use

To clean and remove allergens, wipe surfaces clean with product and let it dry. Can use on non porous surfaces. Kills 99.99% of germs around the home, office and classroom.

Keep out of reach of children. If swallowed, get medical help or contact a Poison Control Center right away.

Warnings

For external use only. Flammable. Keep away from heat or flame

Do not use

- in children less than 2 months of age
- on open skin wounds

Directions

- Spray enough product to cover all surfaces. Wipe clean and let it dry.
- Supervise children under 6 years of age when using this product to avoid swallowing.

Purpose

Antisepticbto help reduce bacteria that potentially can cause disease.

Package Label - Principal Display Panel

473 ml NDC: 79930-7115-4

946 ml NDC: 79930-7115-6

3.79 L NDC: 79930-7115-5